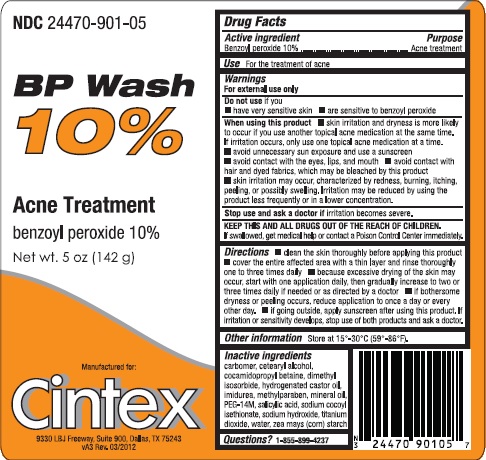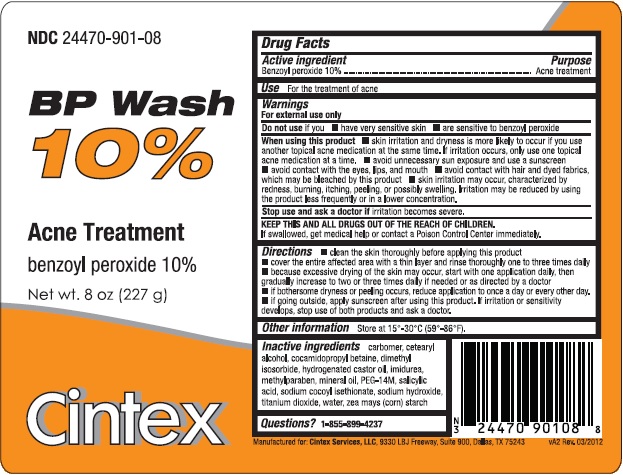 DRUG LABEL: BP Wash
NDC: 24470-901 | Form: EMULSION
Manufacturer: CINTEX SERVICES, LLC
Category: otc | Type: HUMAN OTC DRUG LABEL
Date: 20251218

ACTIVE INGREDIENTS: BENZOYL PEROXIDE 100 mg/1 g
INACTIVE INGREDIENTS: TITANIUM DIOXIDE; COCAMIDOPROPYL BETAINE; MINERAL OIL; POLYETHYLENE OXIDE 600000; HYDROGENATED CASTOR OIL; WATER; CETOSTEARYL ALCOHOL; IMIDUREA; SODIUM COCOYL ISETHIONATE; STARCH, CORN; CARBOXYPOLYMETHYLENE; DIMETHYL ISOSORBIDE; METHYLPARABEN; SALICYLIC ACID; SODIUM HYDROXIDE

BP Wash 10% (benzoyl peroxide 10%)

Active ingredient

Benzoyl peroxide 10%

Purpose

Acne treatment

Use

For the treatment of acne

Warnings

For external use only
Do not use if you

- have very sensitive skin
- are sensitive to benzoyl peroxide

When using this product

- skin irritation and dryness is more likely to occur if you use another topical acne medication at the same time. If irritation occurs, only use one topical acne medication at a time.
- avoid unnecessary sun exposure and use a sunscreen
- avoid contact with the eyes, lips, and mouth
- avoid contact with hair and dyed fabrics, which may be bleached by this product
- skin irritation may occur, characterized by redness, burning, itching, peeling, or possibly swelling. Irritation may be reduced by using the product less frequently or in a lower concentration.

Stop use and ask a doctor if irritation becomes severe.

KEEP OUT OF REACH OF CHILDREN

KEEP THIS AND ALL DRUGS OUT OF THE REACH OF CHILDREN.
If swallowed, get medical help or contact a Poison Control Center immediately.

Directions

- clean the skin thoroughly before applying this product
- cover the entire affected area with a thin layer and rinse thoroughly one to three times daily
- because excessive drying of the skin may occur, start with one application daily, then gradually increase to two or three times daily if needed or as directed by a doctor
- if bothersome dryness or peeling occurs, reduce application to once a day or every other day.
- if going outside, apply sunscreen after using this product. If irritation or sensitivity develops, stop use of both products and ask a doctor.

Other information

Store at 20°C to 25°C (68°F to 77°F), excursions permitted between 15°C and 30°C (between 59°F and 86°F).

Inactive ingredients

carbomer, cetearyl alcohol, cocamidopropyl betaine, dimethyl isosorbide, hydrogenated castor oil, imidurea, methylparaben, mineral oil, PEG-14M, salicylic acid, sodium cocyl isethionate, sodium hydroxide, titanium dioxide, water, zea mays (corn) starch

Questions?

1-855-899-4237